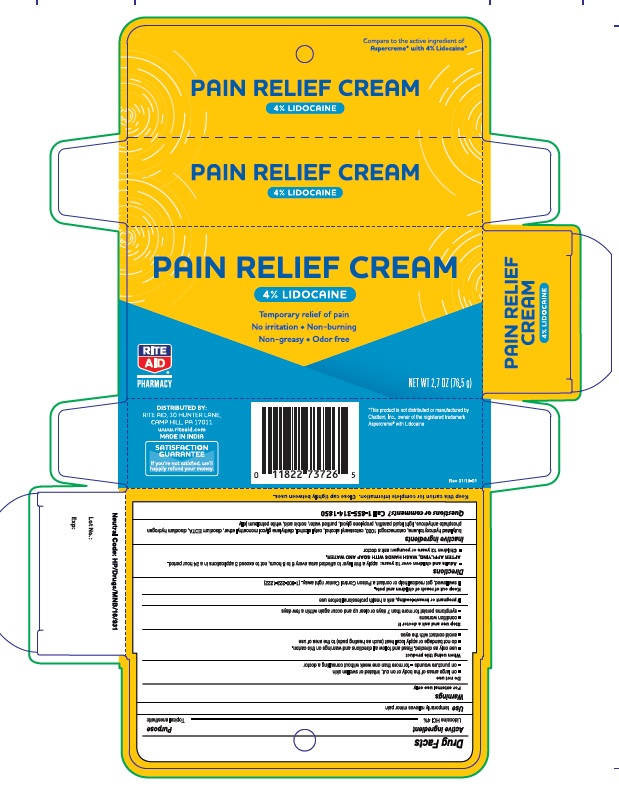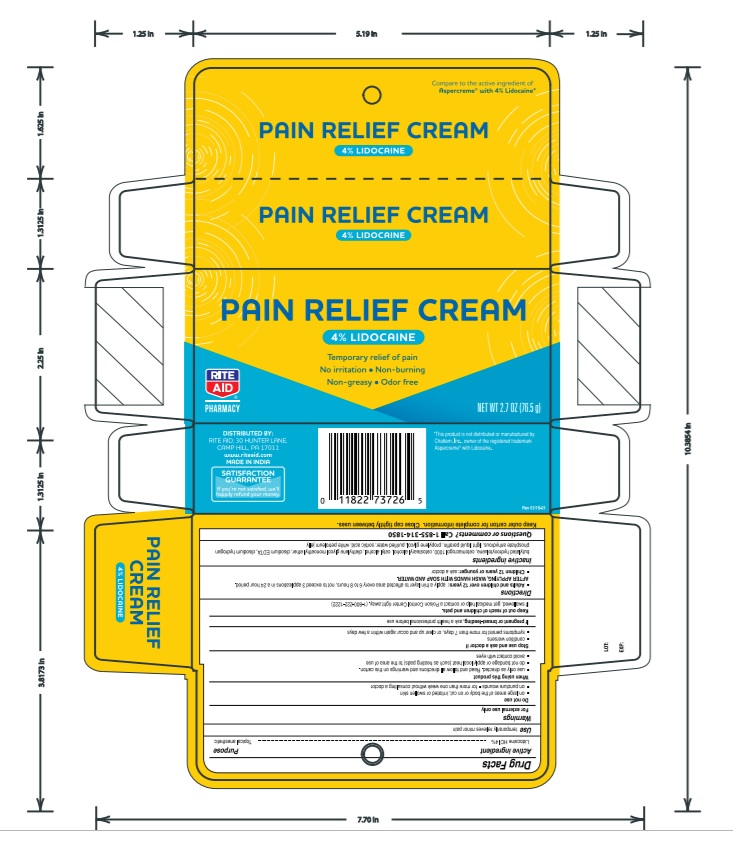 DRUG LABEL: Rite aid Pain Relief Cream Lidocaine 4%
NDC: 76168-315 | Form: CREAM
Manufacturer: Velocity Pharma LLC
Category: otc | Type: HUMAN OTC DRUG LABEL
Date: 20201005

ACTIVE INGREDIENTS: LIDOCAINE HYDROCHLORIDE 4 g/100 g
INACTIVE INGREDIENTS: DIETHYLENE GLYCOL ETHYL METHYL ETHER; WATER; BUTYLATED HYDROXYTOLUENE; CETOSTEARYL ALCOHOL; CETETH-20; CETYL ALCOHOL; EDETATE DISODIUM; SODIUM PHOSPHATE, DIBASIC, ANHYDROUS; LIGHT MINERAL OIL; PROPYLENE GLYCOL; SORBIC ACID; PETROLATUM

Rite aid Pain Relief Cream Lidocaine 4%

Lidocaine Pain Relieving Creme

Drug Facts

Active ingredient

Lidocaine HCI 4%

Purpose

Topical anesthetic

Uses

temporarily relieves minor pain

Warnings

For external use only

Do not use

- on large areas of the body or on cut, irritated or swollen skin
- on puncture wounds
- for more than one week without consulting a doctor

When using this product

- use only as directed. Read and follow all directions and warnings on this carton.
- do not allow contact with the eyes
- do not bandage or apply local heat (such as heating pads) to the area of use

Stop use and ask a doctor if

- condition worsens
- symptoms persist for more than 7 days or clear up and occur again within a few days

If pregnant or breast-feeding,

ask a health professional before use.

Keep out of reach of children and pets.

If swallowed, get medical help or contact a Poison Control Center right away.

Directions

adults and children over 12 years:

- apply a thin layer to affected area every 6 to 8 hours, not to exceed 3 applications in a 24 hour period

children 12 years and younger: ask a doctor

Inactive ingredients

Butylated hydroxyl toluene,cetostearyl alcohol,cetomacrogol 1000,cetyl alcohol,disodium EDTA,disodium hydrogen phosphate,light liquid paraffin,propylene glycol,sorbic acid,transquitol P, white petroleum jelly

Keep Carton As It Contains Important Information

Close cap tightly between uses.